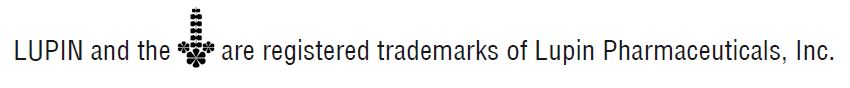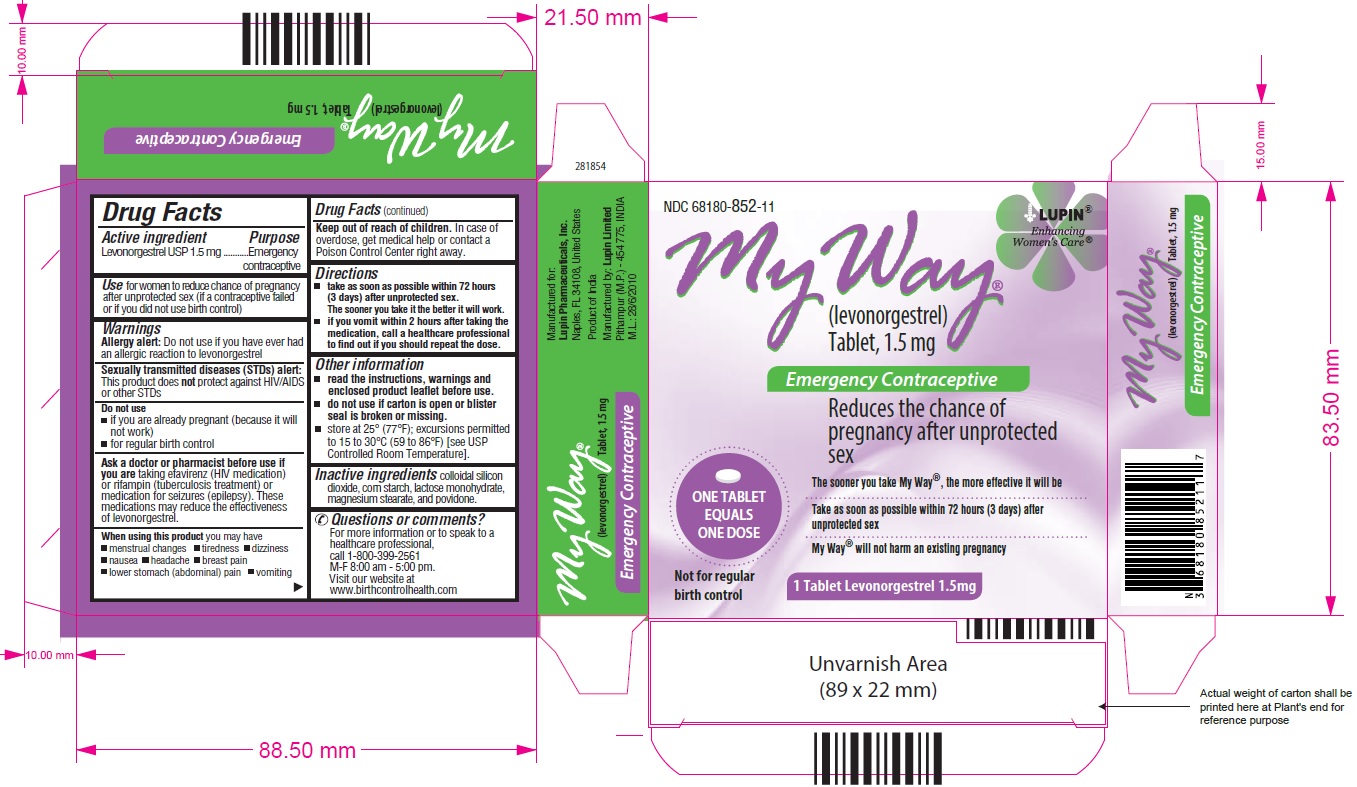 DRUG LABEL: My Way
NDC: 68180-852 | Form: TABLET
Manufacturer: Lupin Pharmaceuticals, Inc.
Category: otc | Type: HUMAN OTC DRUG LABEL
Date: 20251202

ACTIVE INGREDIENTS: LEVONORGESTREL 1.5 mg/1 1
INACTIVE INGREDIENTS: LACTOSE MONOHYDRATE; MAGNESIUM STEARATE; POVIDONE K30; SILICON DIOXIDE; STARCH, CORN

My Way®
(levonorgestrel) Tablet, 1.5 mg

Drug Facts

Active Ingredient

Levonorgestrel USP 1.5 mg

Purpose

Emergency contraceptive

Indications

Use for women to reduce chance of pregnancy after unprotected sex (if a contraceptive failed or if you did not use birth control).

Warnings

Allergy alert: Do not use if you have ever had an allergic reaction to levonorgestrel.

Sexually transmitted diseases (STDs) alert: This product does not protect against HIV/AIDS or other STDs

Do not use

- if you are already pregnant (because it will not work)
- for regular birth control

Ask a doctor or pharmacist before use if you are taking efavirenz (HIV medication) or rifampin (tuberculosis treatment) or medication for seizures (epilepsy). These medications may reduce the effectiveness of levonorgestrel.

When using this product you may have

- menstrual changes
- nausea
- lower stomach (abdominal) pain
- tiredness
- headache
- dizziness
- breast pain
- vomiting

Keep out of the reach of children.

In case of overdose, get medical help or contact a Poison Control center right away.

Directions

- take as soon as possible within 72 hours (3 days) after unprotected sex. The sooner you take it the better it will work.
- if you vomit within 2 hours after taking the medication, call a healthcare professional to find out if you should repeat the dose.

Other Information

- read the instructions, warnings and enclosed product leaflet before use .
- this product works mainly by preventing ovulation (egg release). It may also prevent fertilization of a released egg (joining of sperm and egg) or attachment of a fertilized egg to the uterus (implantation).
- Do not use if carton is open or blister seal is broken or missing .
- store at 25°C (77°C); excursions permitted to 15 to 30°C (59 to 86°C) [see USP Controlled Room temperature].

Inactive Ingredients

colloidal silicon dioxide, corn starch, lactose monohydrate, magnesium stearate, and povidone.

Questions or comments?

For more information or to speak to a healthcare professional, call at 1-800-399-2561 M-F 8:00 am - 5:00 pm or visit our website at www.birthcontrolhealth.com.

My Way®

(levonorgestrel) Tablet, 1.5 mg

Emergency Contraceptive

One Tablet. One Dose.

What You Need to Know

What is My Way®?

My Way is emergency contraception that helps prevent pregnancy after birth control failure or unprotected sex. It is a backup method of preventing pregnancy and should not be used as regular birth control.

What My Way is not.

My Way will not work if you are already pregnant and will not affect an existing pregnancy. My Way will not protect you from HIV infection (the virus that causes AIDS) and other sexually transmitted diseases (STDs).

When should I use My Way?

The sooner you take emergency contraception, the better it works. You should use My Way within 72 hours (3 days) after you have had unprotected sex.

My Way is a backup or emergency method of birth control you can use when:

- your regular birth control was used incorrectly or failed
- you did not use any birth control method

When not to use My Way?

My Way should not be used:

- as a regular birth control method, because it's not as effective as regular birth control.
- if you are already pregnant, because it will not work.
- if you are allergic to levonorgestrel or any other ingredients in My Way.

When should I talk to a doctor or pharmacist?

Ask a doctor or pharmacist before use if you are taking efavirenz (HIV medication) or rifampin (tuberculosis treatment) or medication for seizures (epilepsy). These medications may reduce the effectiveness of My Way and increase your chance of becoming pregnant. Your doctor may prescribe another form of emergency contraception that may not be affected by these medications.

How does My Way work?

My Way works before release of an egg from the ovary. As a result, My Way usually stops or delays the release of an egg from the ovary. My Way is one tablet that contains a higher dose of levonorgestrel than birth control pills and works in a similar way to prevent pregnancy.

How can I get the best results from My Way?

You have 72 hours (3 days) to try to prevent pregnancy after birth control failure or unprotected sex. The sooner you take My Way, the better it works.

How effective is My Way?

If My Way is taken as directed, it can significantly decrease the chance that you will get pregnant. About 7 out of every 8 women who would have gotten pregnant will not become pregnant.

How will I know My Way worked?

You will know My Way has been effective when you get your next period, which should come at the expected time, or within a week of the expected time. If your period is delayed beyond 1 week, it is possible you may be pregnant. You should get a pregnancy test and follow up with your healthcare professional.

Will I experience any side effects?

- some women may have changes in their period, such as a period that is heavier or lighter or a period that is early or late. If your period is more than a week late, you may be pregnant.
- If you have severe abdominal pain, you may have an ectopic pregnancy, and should get immediate medical attention.
- when used as directed, My Way is safe and effective. Side effects may include changes in your period, nausea, lower stomach (abdominal) pain, tiredness, headache, dizziness, and breast tenderness.
- if you vomit within 2 hours of taking the medication, call a healthcare professional to find out if you should repeat the dose.

What if I still have questions about My Way?

If you have questions or need more information, call at 1-800-399-2561 M-F 8:00 am - 5:00 pm or visit our website at www.birthcontrolhealth.com.

Other Information

Keep this and all medication out of reach of children:

In case of overdose, get medical help or contact a Poison Control Center right away at 1-800-222-1222.

Do not use if the seal is opened.

Store at 25°C (77°F); excursions permitted to 15 to 30°C (59 to 86°F) [see USP Controlled Room Temperature].

Active Ingredient: levonorgestrel 1.5 mg

Inactive Ingredients: colloidal silicon dioxide, corn starch, lactose monohydrate, magnesium stearate, and povidone.

My Way® is a registered trademark of Lupin Pharmaceuticals, Inc.

Manufactured for:

Lupin Pharmaceuticals, Inc.

Naples, FL 34108

United States

Manufactured by:

Lupin Limited

Pithampur (M.P.) - 454 775

INDIA

Revised: March 2025 ID#: 279918

If you are sexually active, you should see a healthcare provider for routine checkups. Your healthcare provider will talk to you about and, if necessary, test you for sexually transmitted diseases, teach you about effective methods of routine birth control, and answer any other questions you may have.

PACKAGE LABEL.PRINCIPAL DISPLAY PANEL

My Way®(levonorgestrel) Tablet, 1.5 mg

NDC 68180-852-11

Single Pack- Carton Label: 1 blister containing 1 Tablet